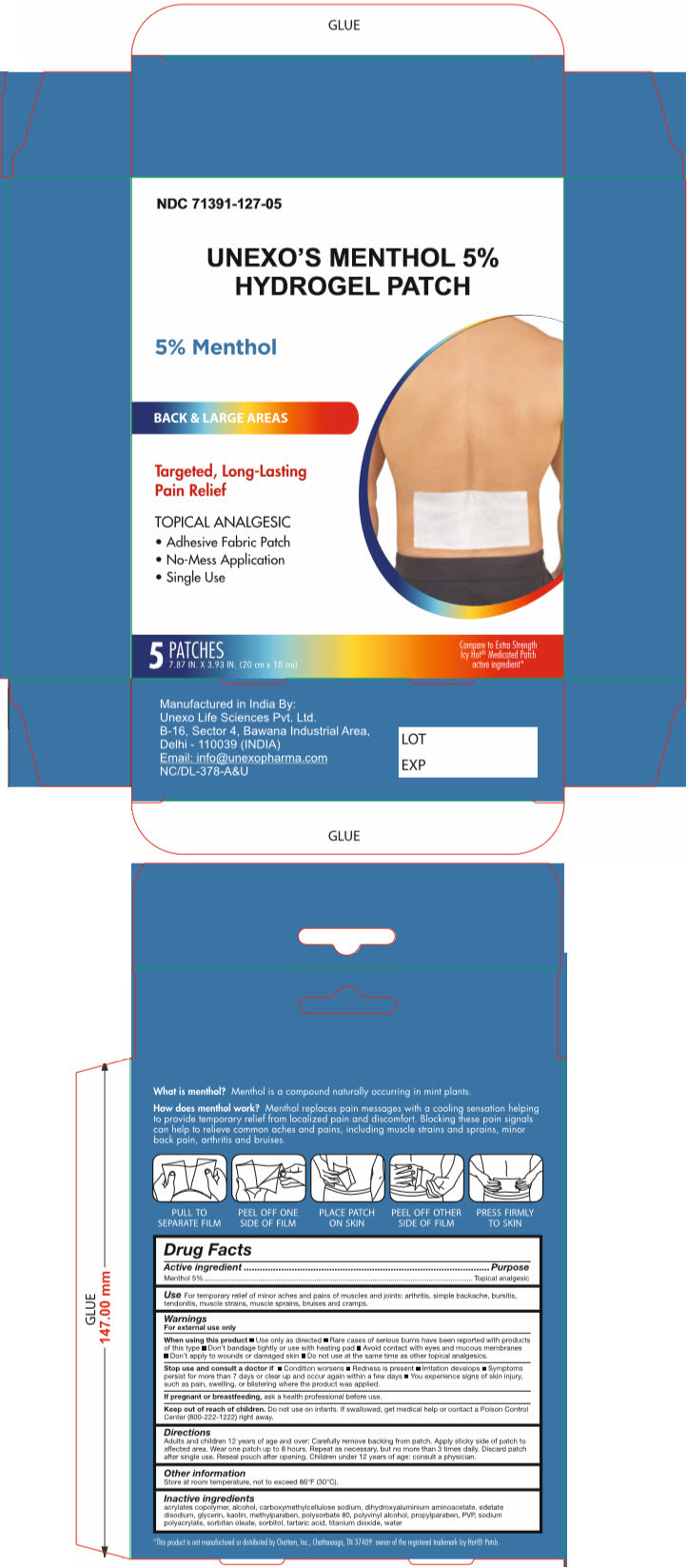 DRUG LABEL: Menthol 5% Hydrogel
NDC: 71391-127 | Form: PATCH
Manufacturer: Unexo Life Sciences, Private Limited
Category: otc | Type: HUMAN OTC DRUG LABEL
Date: 20250110

ACTIVE INGREDIENTS: MENTHOL, UNSPECIFIED FORM 600 mg/1 1
INACTIVE INGREDIENTS: Butyl acrylate/methyl methacrylate/methacrylic acid copolymer (18000 MW); Alcohol; CARBOXYMETHYLCELLULOSE SODIUM, UNSPECIFIED; Edetate disodium; Dihydroxyaluminum aminoacetate; Glycerin; Kaolin; Methylparaben; Polysorbate 80; Polyvinyl alcohol, unspecified; Propylparaben; Povidone, unspecified; Sodium polyacrylate (2500000 MW); Sorbitan monooleate; Sorbitol; Tartaric acid; Titanium dioxide; Water

MENTHOL 5% HYDROGEL PATCH

Drug Facts

Active Ingredient

Menthol 5%

Purpose

Topical Analgesic

Use

For temporary relief of minor aches and pains of muscles and joints: arthritis, simple backache, bursitis, tendonitis, muscle strains, muscle sprains, bruises and cramps

Warnings

For external use only

When using this product

- Use only as directed
- Rare cases of serious burns have been reported with products of this type
- Don't bandage tightly or use with a heating pad
- Avoid contact with eyes or mucous membranes
- Don't apply to wounds or damaged skin
- Do not use at the same time as other topical analgesics

Stop use and consult a doctor if

- Condition worsens
- redness is present
- Irritation develops
- Symptoms persist for more than 7 days or clear up and occur again within a few days
- You experience signs of skin injury such as pain, swelling, or blistering where the product was applied.

PREGNANCY OR BREAST FEEDING

If pregnant of breastfeeding, ask a health professional before use

Keep Out of Reach of Children. Do not use on infants. If swallowed, seek medical help or contact a Poison Control Centre right away.

Directions

- Adults and children 12 years of age and over: Carefully remove backing from patch. Applu sticky side of patch to affected area. Wear one patch up to 8 hours. Repeat as necessary, but no more than 3 times daily. Discard patch after single use. Reseal pouch after opening. Children under 12 years of age consult a physician.

Other Information

Store at room temperature below 86°F (30°C)

Inactive Ingredients

acrylates copolymer, alcohol, carboxymethylcellulose sodium, edetate Disodium, dihydroxyaluminium aminoacetate, glycerine, kaolin, methylparaben, polysorbate 80, polyvinyl alcohol, propylparaben, PVP, sodium polyacrylate, sorbitan oleate, sorbitol, tartaric Acid, titanium Dioxide, water

Manufactured in India By:
Unexo Life Sciences Pvt. Ltd.
B-16, Sector 4, Bawana Industrial Area,
Delhi - 110039 (INDIA)

PRINCIPAL DISPLAY PANEL - 5 Patch Pouch Carton

NDC 71391-127-05

UNEXO'S MENTHOL 5%
HYDROGEL PATCH

5% Menthol

BACK & LARGE AREAS

Targeted, Long-Lasting
Pain Relief

TOPICAL ANALGESIC

- Adhesive Fabric Patch
- No-Mess Application
- Single Use

5
PATCHES
7.87 IN. X 3.93 IN. (20 cm × 10 cm)

Compare to Extra Strength
Icy Hot® Medicated Patch
active ingredient*